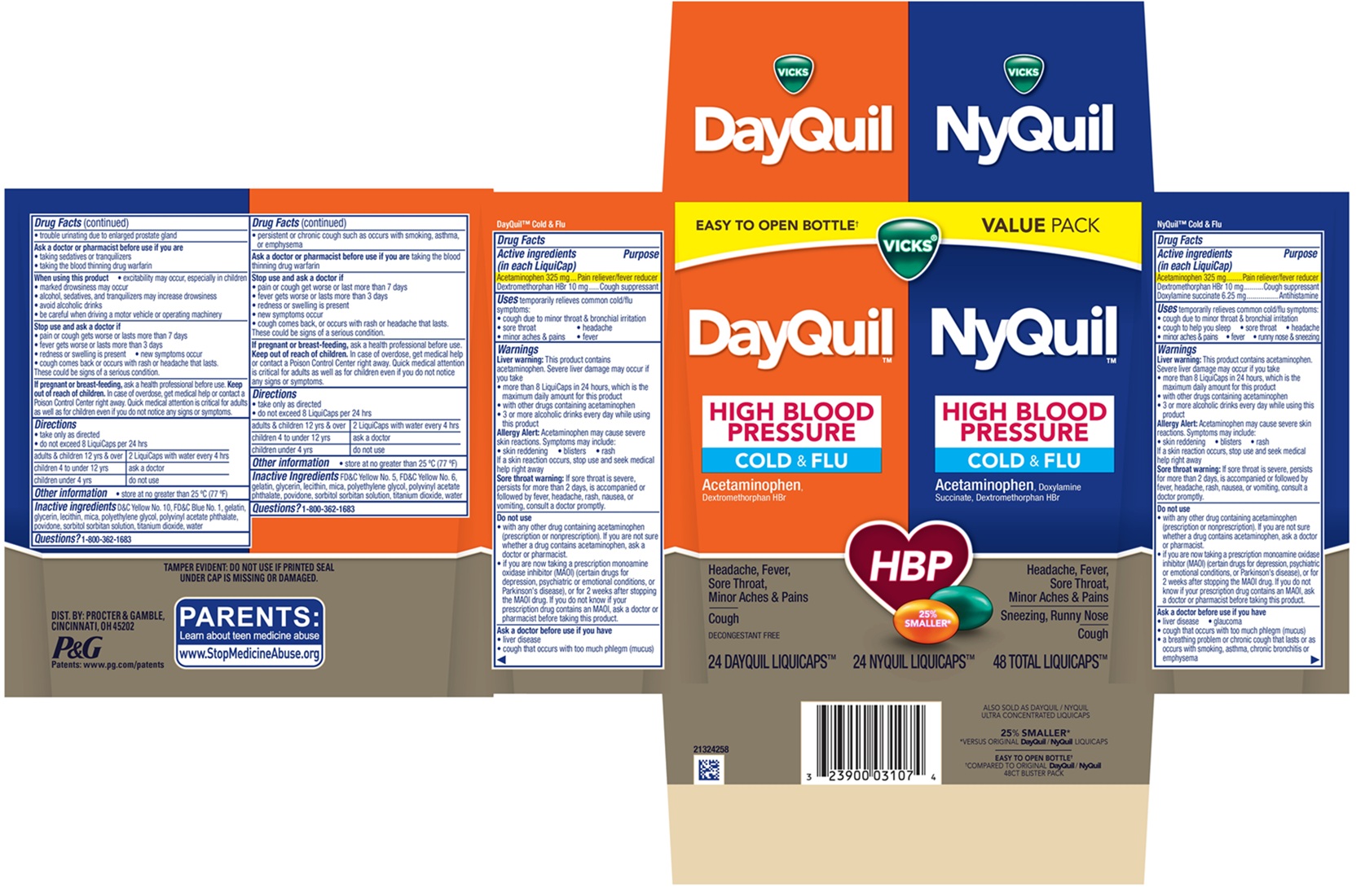 DRUG LABEL: Vicks DayQuil NyQuil
NDC: 69423-805 | Form: KIT | Route: ORAL
Manufacturer: The Procter & Gamble Manufacturing Company
Category: otc | Type: HUMAN OTC DRUG LABEL
Date: 20260219

ACTIVE INGREDIENTS: DEXTROMETHORPHAN HYDROBROMIDE 10 mg/1 1; ACETAMINOPHEN 325 mg/1 1; ACETAMINOPHEN 325 mg/1 1; DOXYLAMINE SUCCINATE 6.25 mg/1 1; DEXTROMETHORPHAN HYDROBROMIDE 10 mg/1 1
INACTIVE INGREDIENTS: POLYVINYL ACETATE PHTHALATE; SORBITOL; GLYCERIN; MICA; FD&C YELLOW NO. 6; POLYETHYLENE GLYCOL, UNSPECIFIED; POVIDONE; WATER; TITANIUM DIOXIDE; FD&C YELLOW NO. 5; GELATIN; LECITHIN, SOYBEAN; POLYETHYLENE GLYCOL, UNSPECIFIED; POVIDONE; D&C YELLOW NO. 10; SORBITOL; MICA; GLYCERIN; WATER; GELATIN; TITANIUM DIOXIDE; FD&C BLUE NO. 1; LECITHIN, SOYBEAN; POLYVINYL ACETATE PHTHALATE

VICKS® DayQuil™ NyQuil™ HIGH BLOOD PRESSURE COLD & FLU, LiquiCaps™
Convenience Pack

VICKS® DayQuil™ HIGH BLOOD PRESSURE COLD & FLU, LiquiCaps™

Drug Facts

DayQuil™ Cold & Flu

Active Ingredient (in each LiquiCap)

Acetaminophen 325 mg

Dextromethorphan HBr 10 mg

Purpose

Pain reliever/fever reducer

Cough suppressant

Uses

temporarily relieves common cold/flu symptoms:

• cough due to minor throat & bronchial irritation
• sore throat • headache • minor aches & pains
• fever

Warnings

Liver warning:

This product contains acetaminophen. Severe liver damage may occur if you take

- more than 8 Liquicaps in 24 hours, which is the maximum daily amount for this product
- with other drugs containing acetaminophen
- 3 or more alcoholic drinks every day while using this product

Allergy Alert:

Acetaminophen may cause severe skin reactions. Symptoms may include:

- skin reddening
- blisters
- rash

If a skin reaction occurs, stop use and seek medical help right away

Sore throat warning:

If sore throat is severe, persists for more than 2 days, is accompanied or followed by fever, headache, rash, nausea, or vomiting, consult a doctor promptly.

Do not use

- with any other drug containing acetaminophen (prescription or nonprescription). If you are not sure whether a drug contains acetaminophen, ask a doctor or pharmacist.
- if you are now taking a prescription monoamine oxidase inhibitor (MAOI) (certain drugs for depression, psychiatric or emotional conditions, or Parkinson's disease), or for 2 weeks after stopping the MAOI drug. If you do not know if your prescription drug contains an MAOI, ask a doctor or pharmacist before taking this product.

Ask a doctor before use if you have

- liver disease
- cough that occurs with too much phlegm (mucus)
- persistent or chronic cough such as occurs with smoking, asthma, or emphysema

Ask a doctor or pharmacist before use if you are

taking the blood thinning drug warfarin

Stop use and ask a doctor if

- pain or cough get worse or last more than 7 days
- fever gets worse or lasts more than 3 days
- redness or swelling is present
- new symptoms occur
- cough comes back, or occurs with rash or headache that lasts.

These could be signs of a serious condition.

If pregnant or breast-feeding,

ask a health professional before use.

Keep out of reach of children.

OVERDOSAGE

In case of overdose, get medical help or contact a Poison Control Center right away. Quick medical attention is critical for adults as well as for children even if you do not notice any signs or symptoms.

Directions

• take only as directed

• do not exceed 8 LiquiCaps per 24 hrs

adults & children 12 yrs & over | 2 LiquiCaps with water every 4 hrs
children 4 to under 12 yrs | ask a doctor
children under 4 yrs | do not use

Other information

store at no greater than 25°C (77°F)

Inactive ingredients

FD&C Yellow No. 5, FD&C Yellow No. 6, gelatin, glycerin, lecithin, mica, polyethylene glycol, polyvinyl acetate phthalate, povidone, sorbitol sorbitan solution, titanium dioxide, water

Questions?

1-800-362-1683

TAMPER EVIDENT: DO NOT USE IF PRINTED SEAL UNDER CAP IS MISSING OR DAMAGED.

DIST. BY PROCTER & GAMBLE,

CINCINNATI OH 45202

VICKS® NyQuil™ HIGH BLOOD PRESSURE COLD & FLU, LiquiCaps™

Drug Facts

NyQuil™ Cold & Flu

Active Ingredient (in each LiquiCap)

Acetaminophen 325 mg

Dextromethorphan HBr 10 mg

Doxylamine succinate 6.25 mg

Purpose

Pain reliever/fever reducer

Cough suppressant

Antihistamine

Uses

temporarily relieves common cold/flu symptoms:

- cough due to minor throat & bronchial irritation
- sore throat
- headache
- minor aches & pains
- fever
- runny nose & sneezing

Warnings

Liver warning:

This product contains acetaminophen. Severe liver damage may occur if you take

- more than 8 Liquicaps in 24 hours, which is the maximum daily amount for this product
- with other drugs containing acetaminophen
- 3 or more alcoholic drinks every day while using this product

Allergy Alert:

Acetaminophen may cause severe skin reactions. Symptoms may include:

- skin reddening
- blisters
- rash

If a skin reaction occurs, stop use and seek medical help right away

Sore throat warning:

If sore throat is severe, persists for more than 2 days, is accompanied or followed by fever, headache, rash, nausea, or vomiting, consult a doctor promptly.

Do not use

- with any other drug containing acetaminophen (prescription or nonprescription). If you are not sure whether a drug contains acetaminophen, ask a doctor or pharmacist.
- if you are now taking a prescription monoamine oxidase inhibitor (MAOI) (certain drugs for depression, psychiatric or emotional conditions, or Parkinson's disease), or for 2 weeks after stopping the MAOI drug. If you do not know if your prescription drug contains an MAOI, ask a doctor or pharmacist before taking this product.

Ask a doctor before use if you have

• liver disease

• glaucoma

• cough that occurs with too much phlegm (mucus)

• a breathing problem or chronic cough that lasts or as occurs with smoking, asthma, chronic bronchitis, or emphysema

• trouble urinating due to enlarged prostate gland

Ask a doctor or pharmacist before use if you are

• taking sedatives or tranquilizers

• taking the blood thinning drug warfarin

When using this product

- excitability may occur, especially in children
- marked drowsiness may occur
- avoid alcoholic drinks
- be careful when driving a motor vehicle or operating machinery
- alcohol, sedatives, and tranquilizers may increase drowsiness

Stop use and ask a doctor if

• pain or cough gets worse or lasts more than 7 days

• fever gets worse or lasts more than 3 days

• redness or swelling is present

• new symptoms occur

• cough comes back or occurs with rash or headache that lasts.

These could be signs of a serious condition.

If pregnant or breast-feeding,

ask a health professional before use.

Keep out of reach of children.

In case of overdose, get medical help or contact a Poison Control Center right away. Quick medical attention is critical for adults as well as for children even if you do not notice any signs or symptoms.

Directions

• take only as directed

• do not exceed 8 LiquiCaps per 24 hrs

adults & children 12 yrs & over | 2 LiquiCaps with water every 4 hrs
children 4 to under 12 yrs | ask a doctor
children under 4 yrs | do not use

Other information

store at no greater than 25°C (77°F)

Inactive ingredients

D&C Yellow No. 10, FD&C Blue No. 1, gelatin, glycerin, lecithin, mica, polyethylene glycol, polyvinyl acetate phthalate, povidone, sorbitol sorbitan solution, titanium dioxide, water

Questions?

1-800-362-1683

TAMPER EVIDENT: DO NOT USE IF PRINTED SEAL UNDER CAP IS MISSING OR DAMAGED.

DIST. BY PROCTER & GAMBLE,

CINCINNATI OH 45202

PRINCIPAL DISPLAY PANEL

MAX STRENGTH

EASY TO OPEN BOTTLE†

VICKS®

DayQuil™

Acetaminophen, Dextromethorphan HBr

Headache, Fever, Sore Throat, Minor Aches & Pains

Cough

DECONGESTANT FREE

NyQuil™ HIGH BLOOD PRESSURE COLD & FLU

Acetaminophen, Doxylamine Succinate, Dextromethorphan HBr

Headache, Fever, Sore Throat, Minor Aches & Pains

Sneezing, Runny Nose

Cough

HBP

25% SMALLER*

24 DAYQUIL LIQUICAPS™ 24 NYQUIL LIQUICAPS™ 48 TOTAL LIQUICAPS™